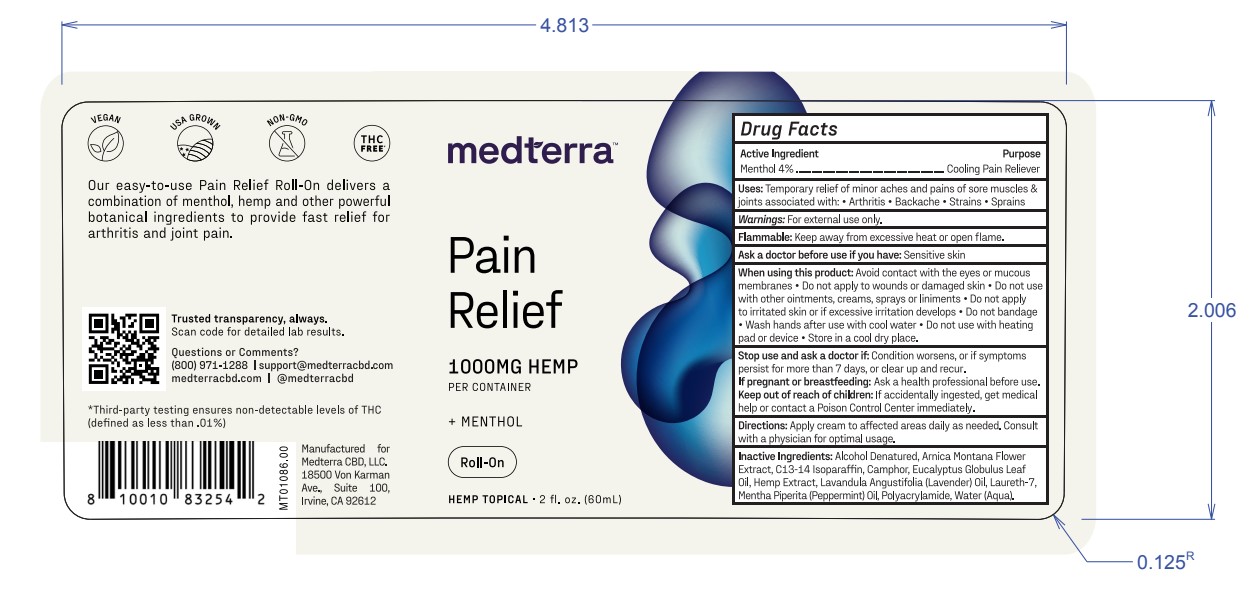 DRUG LABEL: Medterra Pain Relief Menthol Roll-On
NDC: 83696-601 | Form: CREAM
Manufacturer: Respect Manufacturing Corporation
Category: otc | Type: HUMAN OTC DRUG LABEL
Date: 20250623

ACTIVE INGREDIENTS: MENTHOL, UNSPECIFIED FORM 2.36 g/59.1 g
INACTIVE INGREDIENTS: EUCALYPTUS OIL; WATER; PEPPERMINT OIL; CAMPHOR OIL; LAURETH-7; C13-14 ISOPARAFFIN; ALCOHOL; POLYACRYLAMIDE (CROSSLINKED; 0.01-0.2 MOLE PERCENT BISACRYLAMIDE); ARNICA MONTANA FLOWER; HEMP; LAVENDER OIL

Medterra Pain Relief Menthol Roll-On

Active Ingredient

Menthol 4%

Warnings

For external use only.

Purpose

Cooling Pain Reliever

Uses

Temporary relief of minor aches and pains of sore muscles & joints associated with: Arthritis·Backache·Strains·Sprains·

Flammable

Keep away from excessive heat or open flame.

Ask a doctor before use if you have

Sensitive Skin

When using this product:

Avoid contact with the eyes or mucous
membranes • Do not apply to wounds or damaged skin • Do not use
with other ointments, creams, sprays orliniments •Do not apply
to irritated skin orif excessive irritation develops • Do not bandage
• Wash hands after use with cool water • Do not use with heating
pad or device • Store in a cool dry place.

Stop use and ask a doctor if:

Condition worsens, or if symptoms
persist for more than 7 days, or clear up and recur.

If pregnant or breastfeeding:

Ask a health professional before use.

Keep out of reach of children:

If accidentally ingested, get medical help or contact a Poison Control Center immediately.

Directions

Apply cream to affected areas daily as needed. Consult
with a physician for optimal usage.

Inactive Ingredients

Alcohol Denatured, Arnica Montana Flower
Oil, Hemp Extract, Lavandula Angustifolia (Lavender) Oil, Laureth-7,
Polyacrylamide, Water(Aqua).

Questions or Comments?

(800) 971-1288 | supportmedterracbd.com

medterracbd.com | @medterracbd